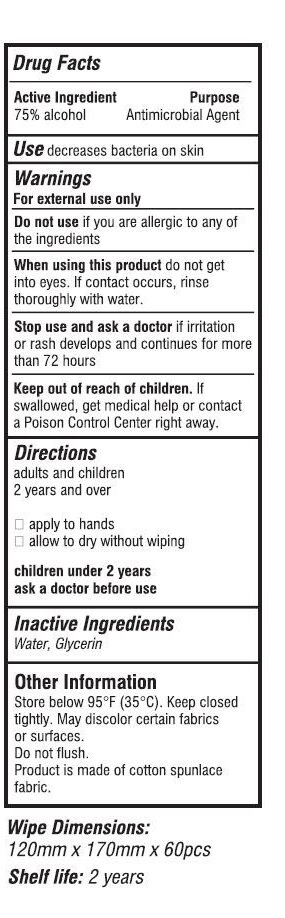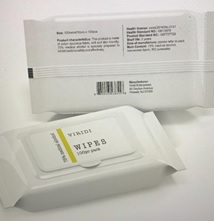 DRUG LABEL: WIPES
NDC: 77451-201 | Form: CLOTH
Manufacturer: Jewellery Time Limited
Category: otc | Type: HUMAN OTC DRUG LABEL
Date: 20200702

ACTIVE INGREDIENTS: ALCOHOL 1 mL/1 1
INACTIVE INGREDIENTS: GLYCERIN; HYDROGEN PEROXIDE; WATER

WIPES

WIPES

Active Ingredient(s)

Alcohol 1mL/pcs. Purpose: Antimicrobial Agent

Purpose

Antimicrobial Agent, WIPES

Use

Wipes to help decreases bacteria on skin. For use when soap and water are not available.

Warnings

For external use only. Flammable. Keep away from heat or flame

Do not use

- in children less than 2 months of age
- on open skin wounds

When using this product keep out of eyes, ears, and mouth. In case of contact with eyes, rinse eyes thoroughly with water.
Stop use and ask a doctor if irritation or rash occurs. These may be signs of a serious condition.
Keep out of reach of children. If swallowed, get medical help or contact a Poison Control Center right away.

Stop use and ask a doctor if irritation or rash occurs. These may be signs of a serious condition.

Keep out of reach of children. If swallowed, get medical help or contact a Poison Control Center right away.

Directions

- Apply to hands. Allow to dry without wiping.
- Supervise children under 6 years of age when using this product to avoid swallowing.

Other information

- Store between 15-30C (59-86F)
- Avoid freezing and excessive heat above 40C (104F)

Inactive ingredients

glycerin, hydrogen peroxide, purified water USP